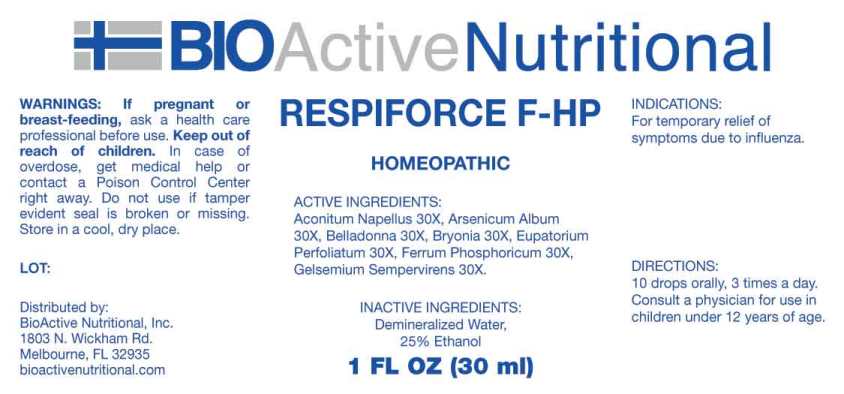 DRUG LABEL: Respiforce
NDC: 43857-0609 | Form: LIQUID
Manufacturer: BioActive Nutritional, Inc.
Category: homeopathic | Type: HUMAN OTC DRUG LABEL
Date: 20240912

ACTIVE INGREDIENTS: ACONITUM NAPELLUS WHOLE 30 [hp_X]/1 mL; ARSENIC TRIOXIDE 30 [hp_X]/1 mL; ATROPA BELLADONNA 30 [hp_X]/1 mL; BRYONIA ALBA ROOT 30 [hp_X]/1 mL; EUPATORIUM PERFOLIATUM FLOWERING TOP 30 [hp_X]/1 mL; FERROSOFERRIC PHOSPHATE 30 [hp_X]/1 mL; GELSEMIUM SEMPERVIRENS ROOT 30 [hp_X]/1 mL
INACTIVE INGREDIENTS: WATER; ALCOHOL

DRUG FACTS:

ACTIVE INGREDIENTS:

Aconitum Napellus 30X, Arsenicum Album 30X, Belladonna 30X, Bryonia (Alba) 30X, Eupatorium Perfoliatum 30X, Ferrum Phosphoricum 30X, Gelsemium Sempervirens 30X.

INDICATIONS:

For temporary relief of symptoms due to influenza.

WARNINGS:

If pregnant or breast-feeding, ask a health care professional before use.

Keep out of reach of children. In case of overdose, get medical help or contact a Poison Control Center right away.

Do not use if tamper evident seal is broken or missing.

Store in a cool, dry place.

KEEP OUT OF REACH OF CHILDREN:

In case of overdose, get medical help or contact a Poison Control Center right away.

DIRECTIONS:

10 drops orally, 3 times a day. Consult a physician for use in children under 12 years of age.

INDICATIONS:

For temporary relief of symptoms due to influenza.

INACTIVE INGREDIENTS:

Demineralized Water, 25% Ethanol

QUESTIONS:

Distributed by:
BioActive Nutritional, Inc.
1803 N. Wickham Rd.
Melbourne, FL 32935
bioactivenutritional.com

PACKAGE LABEL DISPLAY:

BIOActive Nutritional

RESPIFORCE F-HP

HOMEOPATHIC

1 FL OZ (30 ml)